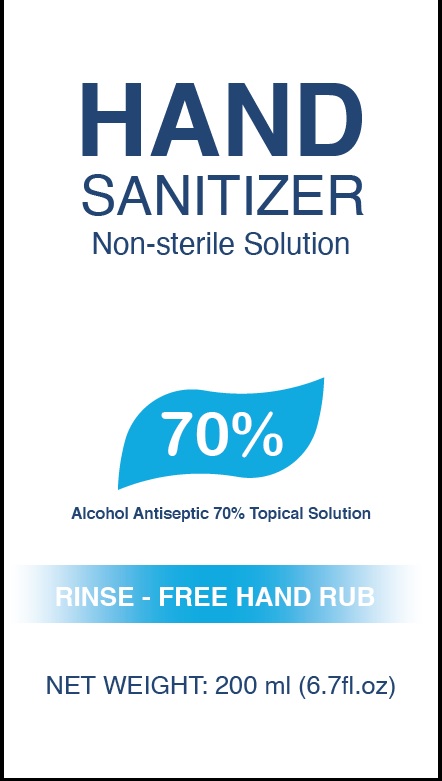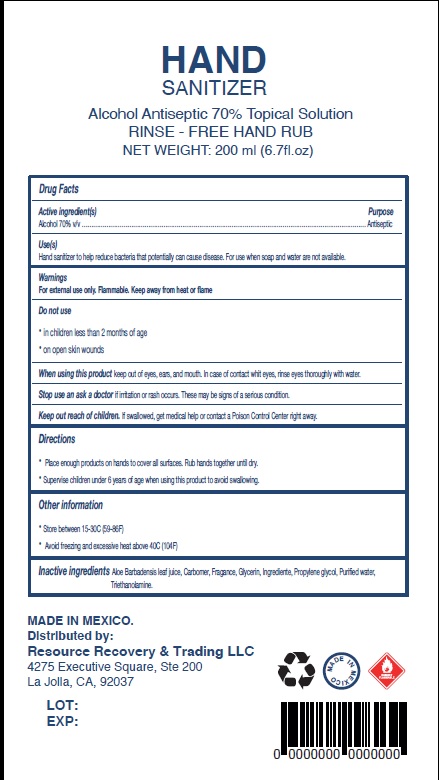 DRUG LABEL: Hand Sanitizer
NDC: 77106-001 | Form: GEL
Manufacturer: Resource Recovery & Trading LLC
Category: otc | Type: HUMAN OTC DRUG LABEL
Date: 20200505

ACTIVE INGREDIENTS: ALCOHOL 70 mL/100 mL
INACTIVE INGREDIENTS: WATER; CARBOMER HOMOPOLYMER, UNSPECIFIED TYPE; TROLAMINE; GLYCERIN; PROPYLENE GLYCOL; ALOE VERA LEAF

Active Ingredient

Ethyl Alcohol 70% v/v.

Purpose

Antiseptic

Uses

to help reduce bacteria on the skin.

Warnings

Flammable. Keep away from heat or flame. For external use only.
When using this product avoid contact with the eyes. If contact occurs, rinse eyes thoroughly with water.
Stop using and ask doctor if irritation or rash appers and lasts.

Keep out of reach of children. If swallowed, get medical help or contact a Poison Control Center right away.

Directions

Apply a small amount in your palm and rub hands together briskly until dry.

Children under 6 should be supervised when using this product.

Other information

Do not store above 110°F (43°C).

Inactive ingredients

Purified water, carbomer, triethanolamine, glycerin, propylene glycol, fragrance, Aloe Barbadensis leaf juice.